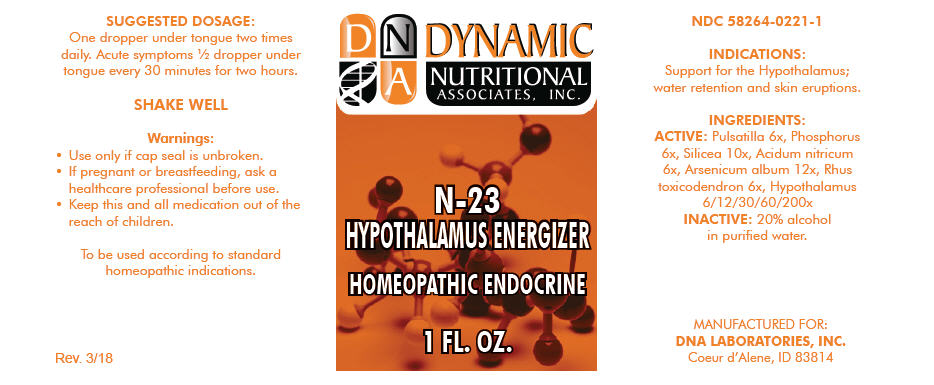 DRUG LABEL: N-23
NDC: 58264-0221 | Form: SOLUTION
Manufacturer: DNA Labs, Inc.
Category: homeopathic | Type: HUMAN OTC DRUG LABEL
Date: 20250109

ACTIVE INGREDIENTS: ANEMONE PULSATILLA 6 [hp_X]/1 mL; PHOSPHORUS 6 [hp_X]/1 mL; SILICON DIOXIDE 10 [hp_X]/1 mL; NITRIC ACID 6 [hp_X]/1 mL; ARSENIC TRIOXIDE 12 [hp_X]/1 mL; TOXICODENDRON PUBESCENS WHOLE 6 [hp_X]/1 mL; BOS TAURUS HYPOTHALAMUS 200 [hp_X]/1 mL
INACTIVE INGREDIENTS: ALCOHOL; WATER

N-23

NDC 58264-0221-1

INDICATIONS

PURPOSE

Support for the Hypothalamus; water retention and skin eruptions.

INGREDIENTS

ACTIVE

Pulsatilla 6x, Phosphorus 6x, Silicea 10x, Acidum nitricum 6x, Arsenicum album 12x, Rhus toxicodendron 6x, Hypothalamus 6/12/30/60/200x

INACTIVE

20% alcohol in purified water.

SUGGESTED DOSAGE

One dropper under tongue two times daily. Acute symptoms ½ dropper under tongue every 30 minutes for two hours.

STORAGE AND HANDLING

SHAKE WELL

Warnings

- Use only if cap seal is unbroken.

PREGNANCY OR BREAST FEEDING

- If pregnant or breastfeeding, ask a healthcare professional before use.

KEEP OUT OF REACH OF CHILDREN

- Keep this and all medication out of the reach of children.

To be used according to standard homeopathic indications.

PRINCIPAL DISPLAY PANEL - 1 FL. OZ. Bottle Label

DYNAMIC
NUTRITIONAL
ASSOCIATES, INC.

N-23
HYPOTHALAMUS ENERGIZER

HOMEOPATHIC ENDOCRINE

1 FL. OZ.